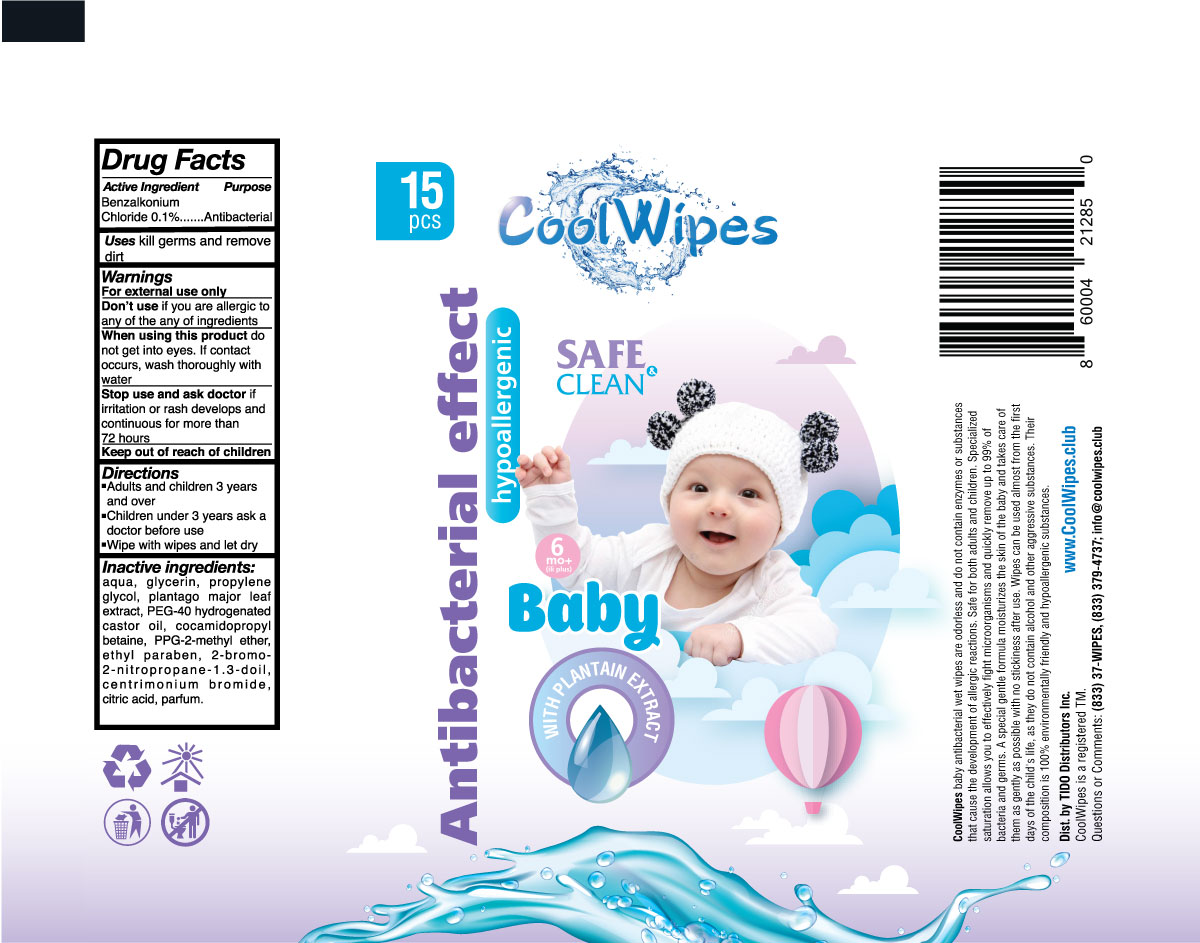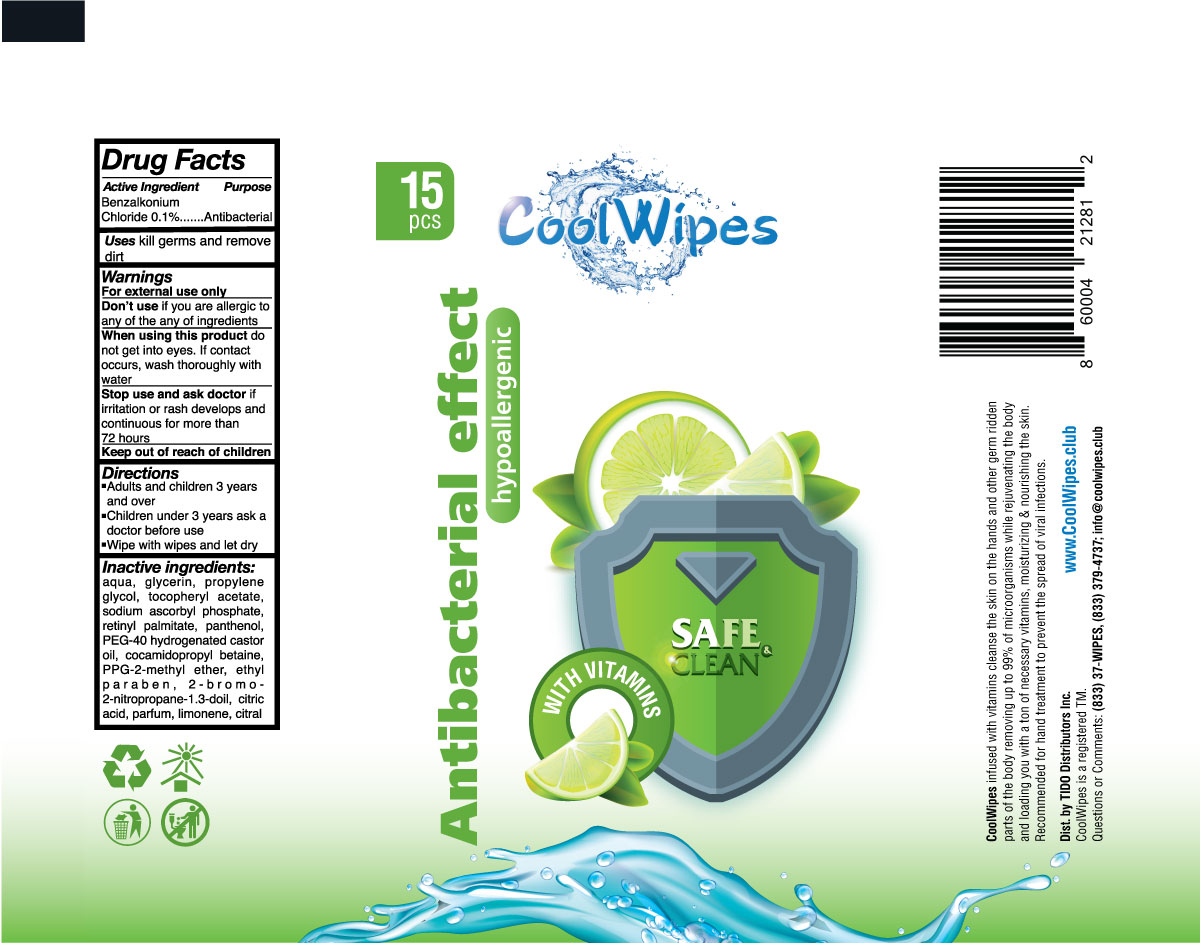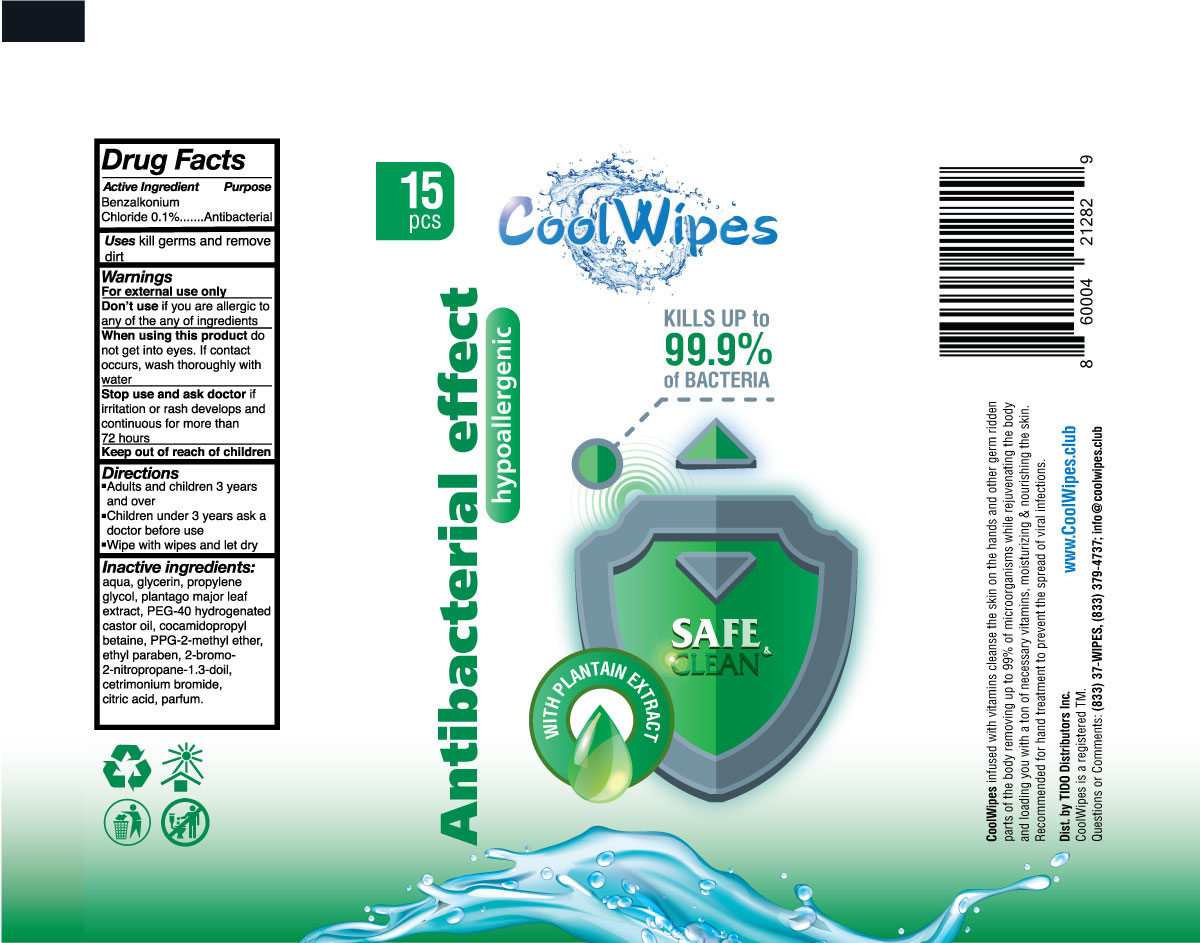 DRUG LABEL: Hand Sanitizer Wipes
NDC: 77848-003 | Form: SOLUTION
Manufacturer: PDD Design LLC
Category: otc | Type: HUMAN OTC DRUG LABEL
Date: 20201205

ACTIVE INGREDIENTS: BENZALKONIUM CHLORIDE 0.1 mg/100 mL
INACTIVE INGREDIENTS: COCAMIDOPROPYL BETAINE; ALPHA-TOCOPHEROL ACETATE; PPG-2 METHYL ETHER; PLANTAGO MAJOR LEAF; ETHYLPARABEN; CETRIMONIUM BROMIDE; CITRIC ACID MONOHYDRATE; GLYCERIN; PROPYLENE GLYCOL; WATER; PEG-40 CASTOR OIL; 2-NITROPROPANE

Active Ingredient(s)

Benzalkonium Chloride 0.1% v/v. Purpose: Antimicrobial

Purpose

Antimicrobial

Use

Kill germs and remove dirt

Warnings

For external use only.

Do not use

if you are allergic to any of ingredients

When using this product do not get into eyes. If contact occurs, wash thoroughly with water

Stop use and ask a doctor if irritation or rash develops and continuous for more than 72 hours

Keep out of reach of children.

Directions

Adults and children 3 years and over

Children under 3 years ask a doctor before use

Wipe with wipes and let dry

Other information

- Store between 15-30C (59-86F)
- Avoid freezing and excessive heat above 40C (104F)

Cool Wipes Baby with Plantain Extract - Inactive Ingredients

Water, Glycerin, Propylene glycol, Plantago Major Leaf, Peg-40 Hydrogenated Castor Oil, Cocamidopropyl Betaine, PPG-2 Methyl Ether, Ethylparaben, 2-Bromo-2-Nitropropane- 1,3-Diol, Ethylparaben, Cetrimonium Bromide, Citric Acid, Parfum

Cool Wipes Safe Clean enriched with vitamins - Inactive ingredients

Water, Glycerin, Propylene glycol, Tocopheryl acetate, Sodium Ascorbyl Phosphate, Retinyl Palmitate, Panthenol, Peg-40 Hydrogenated Castor Oil, Cocamidopropyl Betaine, PPG-2 Methyl Ether, Ethylparaben, 2-Bromo-2-Nitropropane- 1,3-Diol, Citric Acid, Parfum, Limonene, Citral

Cool Wipes Safe Clean enriched with plantain extract

Water, Glycerin, Propylene glycol, Plantago Major Leaf, Peg-40 Hydrogenated Castor Oil, Cocamidopropyl Betaine, PPG-2 Methyl Ether, Ethylparaben, 2-Bromo-2-Nitropropane- 1,3-Diol, Ethylparaben, Cetrimonium Bromide, Citric Acid, Parfum

Cool Wipes Safe Clean enriched with plantain extract - Package Label

15 Wipes NDC:77848-001-15

Cool Wipes Safe Clean enriched with vitamins - Package Label

15 Wipes NDC: 77848-002-15

Cool Wipes Baby with Plantain Extract - Package Label

15 wipes NDC: 77848-003-15